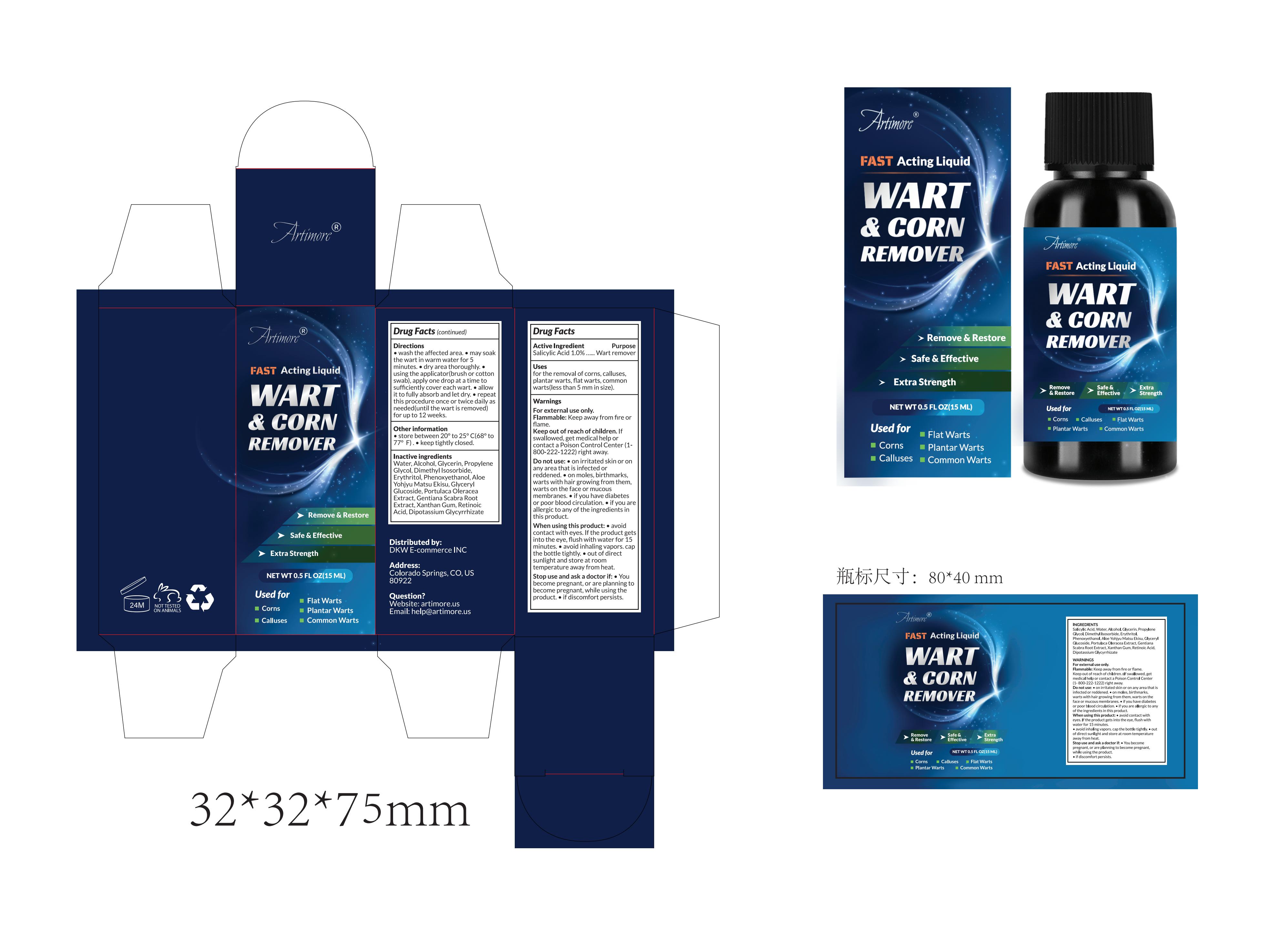 DRUG LABEL: Wart Corn Remover Liquid
NDC: 83871-002 | Form: LIQUID
Manufacturer: IBP CORP CO. LTD.
Category: otc | Type: HUMAN OTC DRUG LABEL
Date: 20240114

ACTIVE INGREDIENTS: SALICYLIC ACID 1 g/100 mL
INACTIVE INGREDIENTS: ALOE; PROPYLENE GLYCOL; ERYTHRITOL; GLYCERIN; WATER; DIMETHYL ISOSORBIDE; PHENOXYETHANOL; GLYCERYL 1,2-DIOLEATE, (S)-; ALCOHOL

83871-002

Active Ingredient

Salicylic Acid 1.0%

Purpose

Wart remover

Use

for the removal of corns, calluses, plantar warts, flat warts, common warts(less than 5 mm in size).

Warnings

For external use only.
Flammable: Keep away from fire or flame.
Keep out of reach of children. If swallowed, get medical help or contact a Poison Control Center (1- 800-222-1222) right away.

Do not use

• on irritated skin or on any area that is infected or reddened.

• on moles, birthmarks, warts with hair growing from them, warts on the face or mucous membranes.

• if you have diabetes or poor blood circulation.

• if you are allergic to any of the ingredients in this product.

When Using

• avoid contact with eyes. If the product gets into the eye, flush with water for 15 minutes.

• avoid inhaling vapors. cap the bottle tightly.

• out of direct sunlight and store at room temperature away from heat.

Stop Use

Stop use and ask a doctor:

• If you become pregnant, or are planning to become pregnant, while using the product.

• if discomfort persists.

Keep Oot Of Reach Of Children

Keep out of reach of children. If swallowed, get medical help or contact a Poison Control Center (1- 800-222-1222) right away.

Directions

• wash the affected area.

• may soak the wart in warm water for 5 minutes.

• dry area thoroughly.

• using the applicator(brush or cotton swab), apply one drop at a time to sufficiently cover each wart.

• allow it to fully absorb and let dry.

• repeat this procedure once or twice daily as needed(until the wart is removed) for up to 12 weeks.

Other information

• store between 20° to 25° C(68° to 77° F) .

• keep tightly closed.

Inactive ingredients

Water, Alcohol, Glycerin, Propylene Glycol, Dimethyl Isosorbide, Erythritol, Phenoxyethanol, Aloe Yohjyu Matsu Ekisu, Glyceryl Glucoside, Portulaca Oleracea Extract, Gentiana Scabra Root Extract, Xanthan Gum, Retinoic Acid, Dipotassium Glycyrrhizate

Questions

Website: artimore.us
Email: help@artimore.us